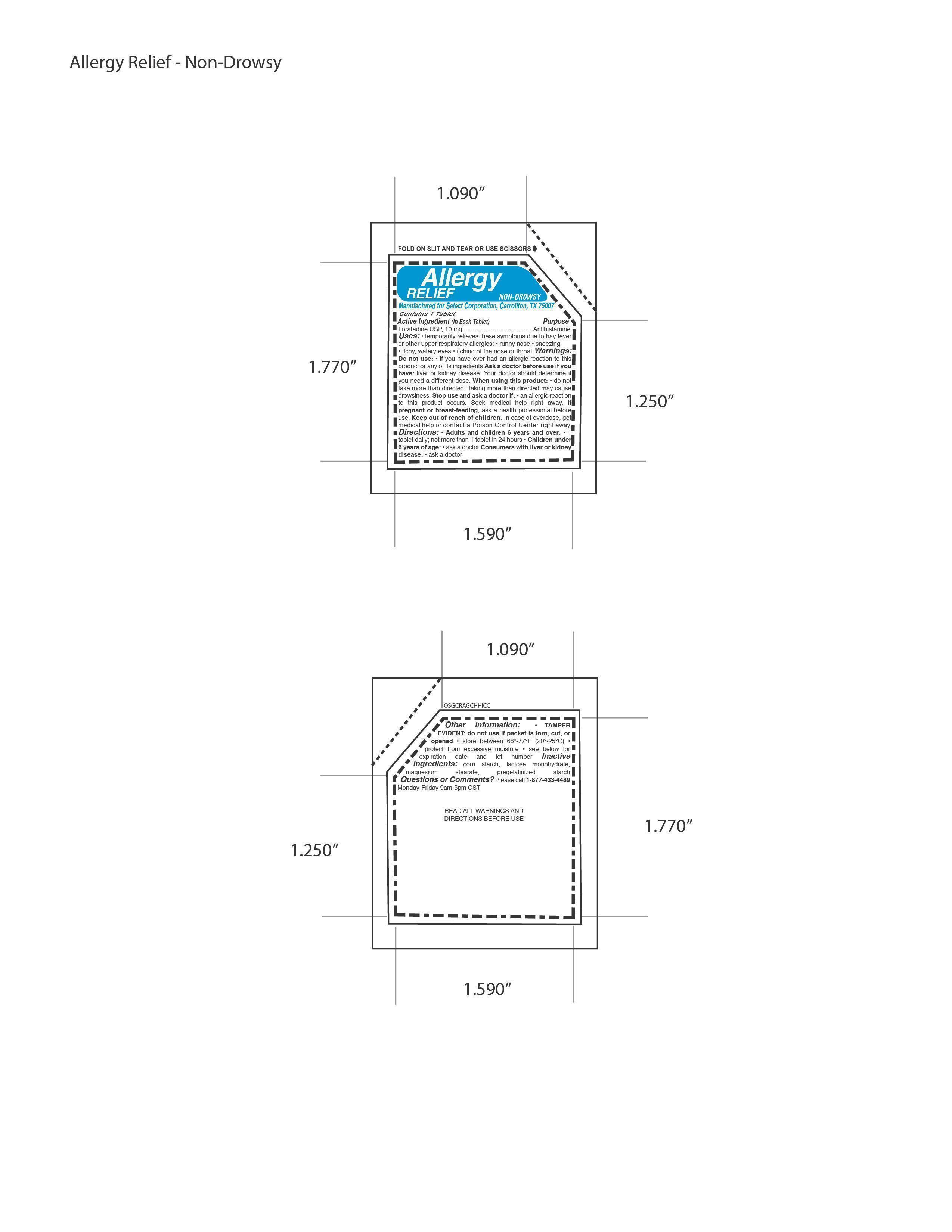 DRUG LABEL: Allergy Relief Non Drowsy
NDC: 52904-430 | Form: TABLET
Manufacturer: Select Corporation
Category: otc | Type: HUMAN OTC DRUG LABEL
Date: 20121015

ACTIVE INGREDIENTS: LORATADINE 10 mg/1 1
INACTIVE INGREDIENTS: MAGNESIUM STEARATE; LACTOSE; STARCH, CORN

Drug Facts

Active Ingredients

Loratadine USP 10 mg

PURPOSE

Antihistamine

DOSAGE AND ADMINISTRATION

Directions: • Adults and children 6 years and over: • 1
tablet daily; not more than 1 tablet in 24 hours • Children under
6 years of age: • ask a doctor

INDICATIONS AND USAGE

Uses: • temporarily relieves these symptoms due to hay fever
or other upper respiratory allergies: • runny nose • sneezing
• itchy, watery eyes • itching of the nose or throat

Warnings:
Do not use: • if you have ever had an allergic reaction to this
product or any of its ingredients Ask a doctor before use if you
have: liver or kidney disease. Your doctor should determine if
you need a different dose. When using this product: • do not
take more than directed. Taking more than directed may cause
drowsiness. Stop use and ask a doctor if: • an allergic reaction
to this product occurs. Seek medical help right away.

PREGNANCY OR BREAST FEEDING

If pregnant or
breast-feeding, ask a health professional before use.

KEEP OUT OF REACH OF CHILDREN.

Inactive
ingredients: corn starch, lactose monohydrate,
magnesium stearate, pregelatinized starch

PACKAGE LABEL

MM1